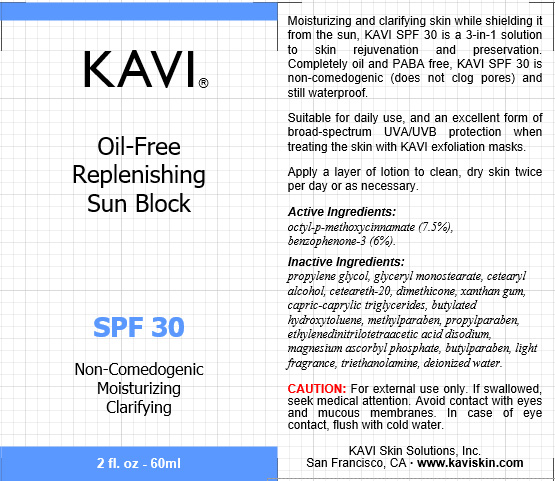 DRUG LABEL: SPF 30
NDC: 42771-0010 | Form: CREAM
Manufacturer: KAVI Skin Solutions, Inc.
Category: otc | Type: HUMAN OTC DRUG LABEL
Date: 20210505

ACTIVE INGREDIENTS: OCTINOXATE 4.5 g/100 g; ZINC OXIDE 3.6 g/100 g
INACTIVE INGREDIENTS: POLYOXYL 20 CETOSTEARYL ETHER 1.8 g/100 g; CETOSTEARYL ALCOHOL 1.8 g/100 g; XANTHAN GUM 0.3 g/100 g; TRICAPRIN 0.12 g/100 g; PROPYLENE GLYCOL 3 g/100 g; GLYCERYL MONOSTEARATE 1.8 g/100 g; DIMETHICONE 1.2 g/100 g; BUTYLATED HYDROXYTOLUENE 0.06 g/100 g

SPF 30

DESCRIPTION

Moisturizing and clarifying skin while shielding it from the sun, KAVI SPF 30 is a 3-in-1 solution to skin rejuvenation and preservation. Completely oil and PABA free, KAVI SPF 30 is non-comedogenic (does not clog pores) and still waterproof.
Suitable for daily use, and an excellent form of broad-spectrum UVA/UVB protection when treating the skin with KAVI exfoliation masks.
Apply a layer of lotion to clean, dry skin twice per day or as necessary.

Active Ingredients

octyl-p-methoxycinnamate (7.5%),
benzophenone-3 (6%).

CAUTION

For external use only. If swallowed, seek medical attention. Avoid contact with eyes and mucous membranes. In case of eye contact, flush with cold water.

Back Panel

Moisturizing and clarifying skin while shielding it from the sun, KAVI SPF 30 is a 3-in-1 solution to skin rejuvenation and preservation. Completely oil and PABA free, KAVI SPF 30 is non-comedogenic (does not clog pores) and still waterproof.
Suitable for daily use, and an excellent form of broad-spectrum UVA/UVB protection when treating the skin with KAVI exfoliation masks.
Apply a layer of lotion to clean, dry skin twice per day or as necessary.

Active Ingredients:
octyl-p-methoxycinnamate (7.5%),
benzophenone-3 (6%).

Inactive Ingredients:
propylene glycol, glyceryl monostearate, cetearyl alcohol, ceteareth-20, dimethicone, xanthan gum, capric-caprylic triglycerides, butylated hydroxytoluene, methylparaben, propylparaben, ethylenedinitrilotetraacetic acid disodium, magnesium ascorbyl phosphate, butylparaben, light fragrance, triethanolamine, deionized water.

CAUTION: For external use only. If swallowed, seek medical attention. Avoid contact with eyes and mucous membranes. In case of eye contact, flush with cold water.

KAVI Skin Solutions, Inc.
San Francisco, CA · www.kaviskin.com